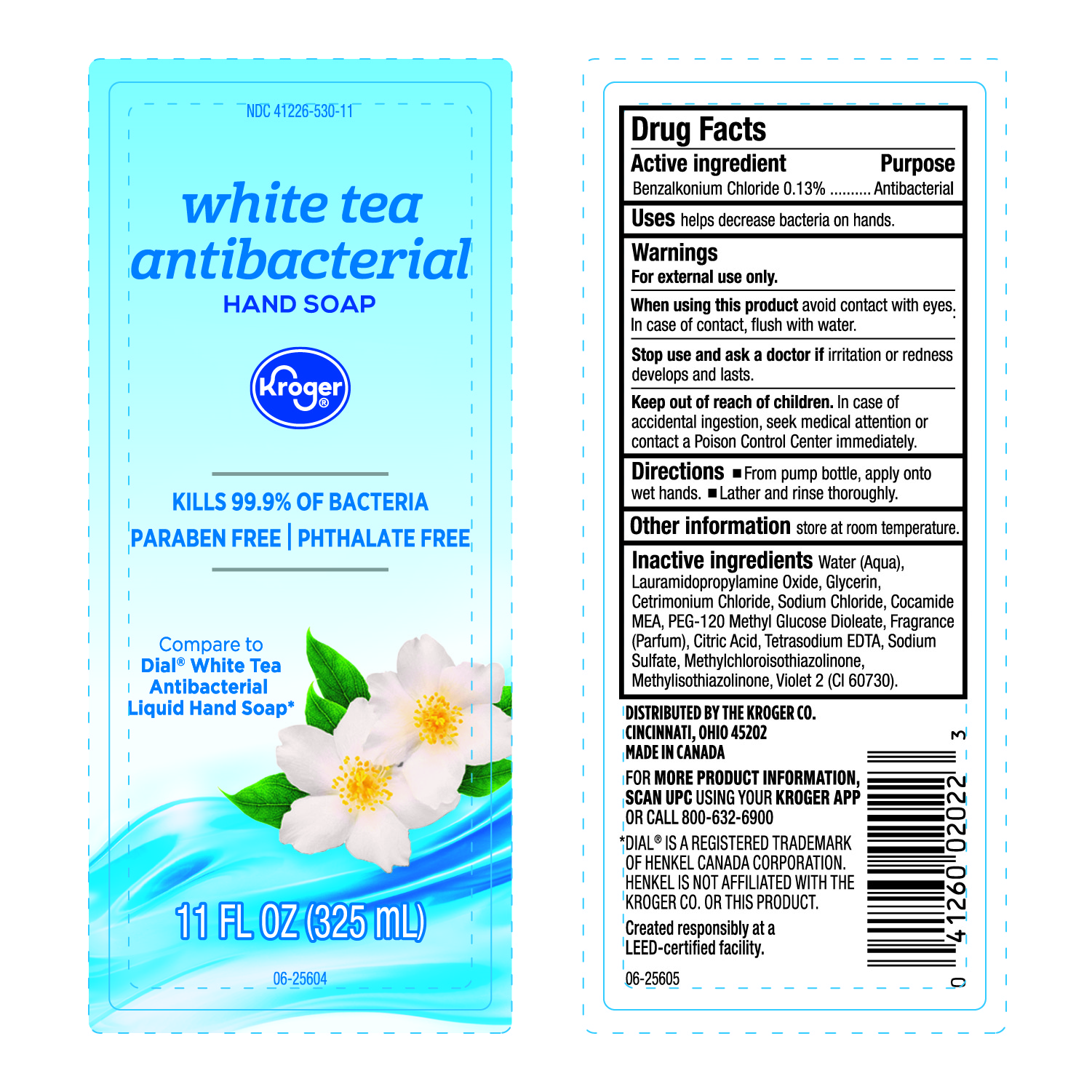 DRUG LABEL: Kroger Antibacterial
NDC: 41226-530 | Form: LIQUID
Manufacturer: Kroger Company
Category: otc | Type: HUMAN OTC DRUG LABEL
Date: 20240224

ACTIVE INGREDIENTS: BENZALKONIUM CHLORIDE 130 mg/100 mL
INACTIVE INGREDIENTS: COCO MONOETHANOLAMIDE; EXT. D&C VIOLET NO. 2; EDETATE SODIUM; METHYLISOTHIAZOLINONE; SODIUM SULFATE; CITRIC ACID MONOHYDRATE; LAURAMIDOPROPYLAMINE OXIDE; SODIUM CHLORIDE; METHYLCHLOROISOTHIAZOLINONE; FRAGRANCE CLEAN ORC0600327; GLYCERIN; CETRIMONIUM CHLORIDE; PEG-120 METHYL GLUCOSE DIOLEATE; WATER

Antibacterial White Tea Liquid Hand Soap

Active Ingredient

Benzalkonium Chloride 0.13%

Purpose

Antibacterial

Uses

Hrlps eliminate bacteria on hands

Warnings

For external use only

When using the product

Avoid contact with eyes. In case of contact flush with water.

Stop use and ask a doctor

If irritation or redness develops and Lasts.

Keep out of reach of children

In case of accidental ingestion, seek medical attention or contact a Poison Control Center immediately.

Directions

- From Pump bottle, apply onto wet hands.
- Lather and rinse thoroughly.

Other Information

Store at room temperature.

Inactive Ingredients

Water (Aqua), Lauramidopropylamine Oxide, Glycerin, Cetrimonium Chloride, Sodium Chloride, Cocamide MEA, PEG-120 Methyl Glucose Dioleate, Fragrance (Parfum), Citric Acid, Tetrasodium EDTA, Sodium Sulfate, Methylchloroisothiazolinone, Methylisothiazolinone, Violet 2 (CI 60730).